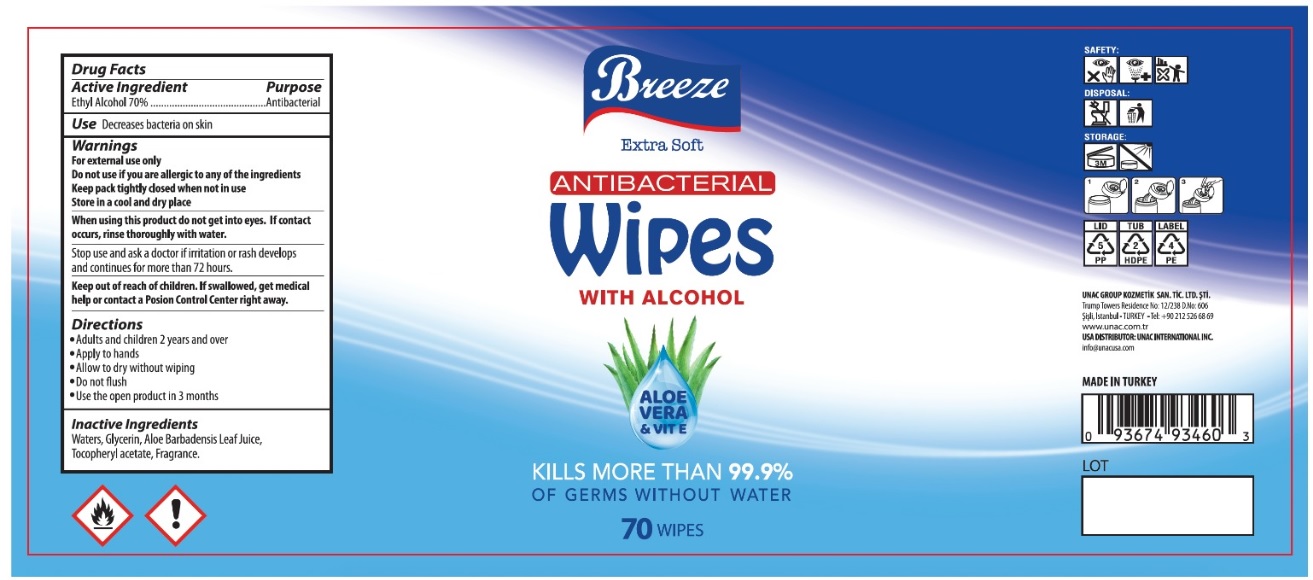 DRUG LABEL: Breeze
NDC: 74955-028 | Form: CLOTH
Manufacturer: COSMOLIVE KOZMETIK SANAYI VE TICARET ANONIM SIRKETI
Category: otc | Type: HUMAN OTC DRUG LABEL
Date: 20200902

ACTIVE INGREDIENTS: ALCOHOL 70 g/100 g
INACTIVE INGREDIENTS: WATER; GLYCERIN; ALOE VERA LEAF; .ALPHA.-TOCOPHEROL ACETATE

Breeze ANTIBACTERIAL Wipes with ALCOHOL

Active Ingredient

Ethyl Alcohol 70%

Purpose

Antibacterial

INDICATIONS AND USAGE

Use Decreases bacteria on skin

Warnings

For external use only

Do not use if you are allergic to any of the ingredients

Keep pack tightly closed when not in use

Store in a cool and dry place

When using this product do not get into eyes. If contact occurs, rinse thoroughly with water.

Stop use and ask a doctor if irritation or rash develops and continues for more than 72 hours.

Keep out of reach of children. If swallowed, get medical help or contact a Poison Control Center right away.

Directions

• Adults and children 2 years and over

• Apply to hands

• Allow to dry without wiping

• Do not flush

• Use the open product in 3 months

Inactive Ingredients

Waters, Glycerin, Aloe Barbadensis Leaf Juice, Tocopheryl acetate, Fragrance.

Extra Soft

WITH ALCOHOL

ALOE VERA & VIT E

KILLS MORE THAN 99.9% OF GERMS WITHOUT WATER

UNAC GROUP KOZMETİK SAN. TİC. LTD. ŞTİ

Trump Towers Residence No: 12/238 D.No:606

Şişli, Istanbul- TURKEY - Tel: +90 212 526 68 69

www.unac.com.tr

USA DISTRIBUTOR: UNAC INTERNATIONAL INC.

info@unacusa.com

MADE IN TURKEY